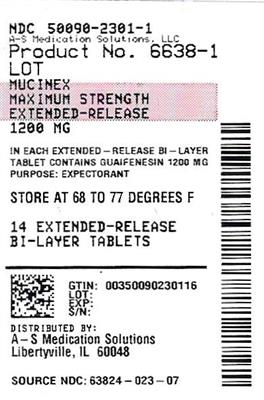 DRUG LABEL: Mucinex
NDC: 50090-2301 | Form: TABLET, EXTENDED RELEASE
Manufacturer: A-S Medication Solutions
Category: otc | Type: HUMAN OTC DRUG LABEL
Date: 20250609

ACTIVE INGREDIENTS: GUAIFENESIN 1200 mg/1 1
INACTIVE INGREDIENTS: CARBOMER HOMOPOLYMER TYPE B (ALLYL PENTAERYTHRITOL CROSSLINKED); CI 42090; ALUMINA; HYDROXYPROPYL METHYLCELLULOSE; MAGNESIUM STEARATE; MICROCRYSTALLINE CELLULOSE

MUCINEX MAXIMUM STRENGTH

Drug Facts

Active ingredient (in each extended-release tablet)

Guaifenesin 1200 mg

Purpose

Expectorant

Uses

- helps loosen phlegm (mucus) and thin bronchial secretions to rid the bronchial passageways of bothersome mucus and make coughs more productive

Warnings

Do not use

- for children under 12 years of age

Ask a doctor before use if you have

- persistent or chronic cough such as occurs with smoking, asthma, chronic bronchitis, or emphysema
- cough accompanied by too much phlegm (mucus)

Stop use and ask a doctor if

- cough lasts more than 7 days, comes back, or occurs with fever, rash, or persistent headache. These could be signs of a serious illness.

PREGNANCY OR BREAST FEEDING

If pregnant or breast-feeding,ask a health professional before use.

Keep out of reach of children.In case of overdose, get medical help or contact a Poison Control Center right away.

Directions

- do not crush, chew, or break extended-release tablet
- take with a full glass of water
- this product can be administered without regard for the timing of meals
- adults and children 12 years of age and over: 1 extended-release tablet every 12 hours. Do not exceed 2 extended-release tablets in 24 hours.
- children under 12 years of age: do not use

Other information

- store at 20-25°C (68-77°F)

Inactive ingredients

carbomer homopolymer type B; FD&C blue no. 1 aluminum lake; hypromellose, USP; magnesium stearate, NF; microcrystalline cellulose, NF; sodium starch glycolate, NF

Questions?

1-866-MUCINEX (1-866-682-4639)

Dist. by: RB Health (US)
Parsippany, NJ 07054-0224

Made in England

HOW SUPPLIED

Product: 50090-2301

NDC: 50090-2301-1 7 TABLET, EXTENDED RELEASE in a BLISTER PACK / 2 in a CARTON